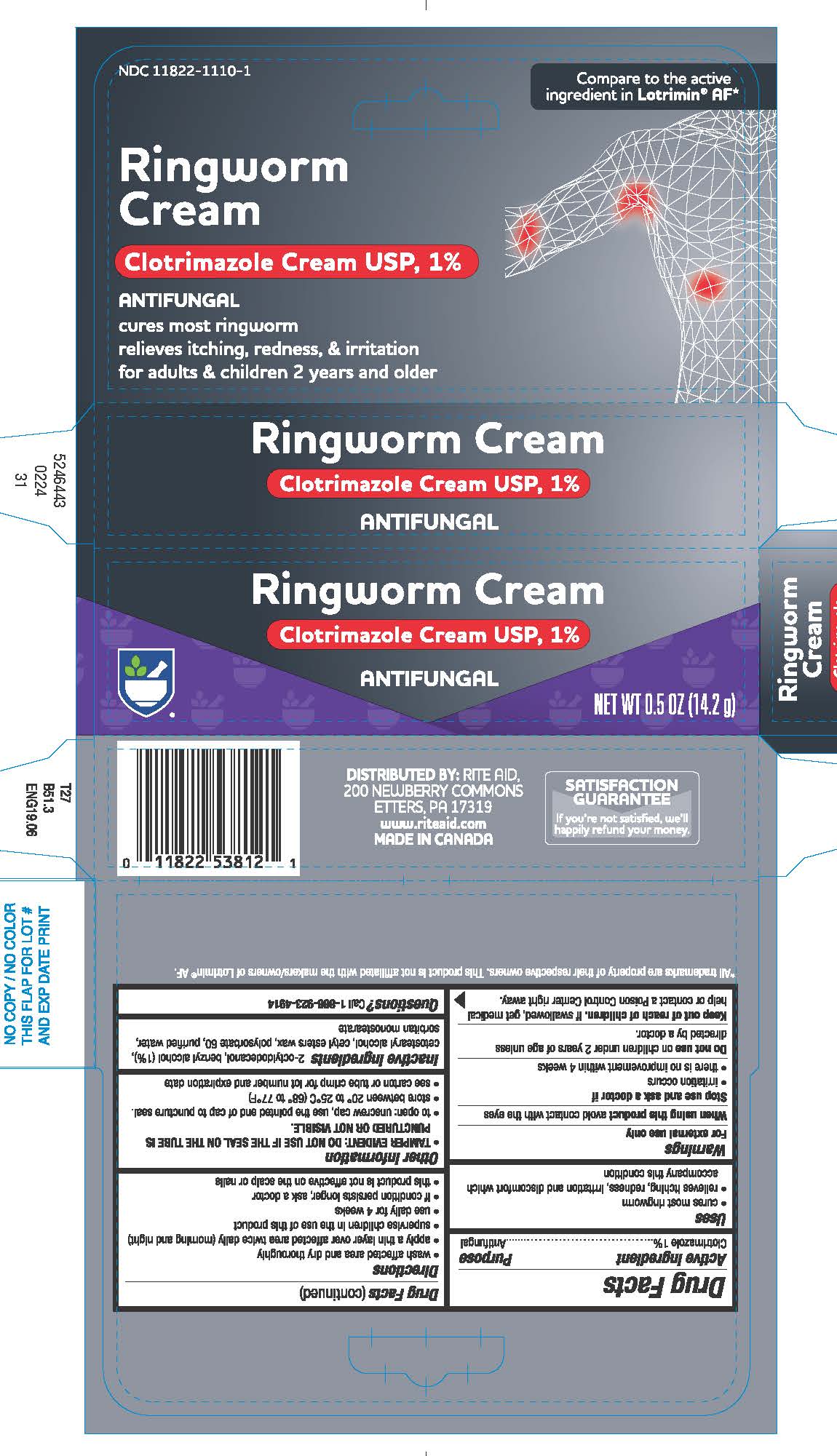 DRUG LABEL: Rite Aid

NDC: 11822-1110 | Form: CREAM
Manufacturer: Rite Aid Corporation
Category: otc | Type: HUMAN OTC DRUG LABEL
Date: 20250708

ACTIVE INGREDIENTS: CLOTRIMAZOLE 1 g/100 g
INACTIVE INGREDIENTS: OCTYLDODECANOL; POLYSORBATE 60; WATER; SORBITAN MONOSTEARATE; BENZYL ALCOHOL; CETOSTEARYL ALCOHOL; CETYL ESTERS WAX

Rite Aid®
antifungal ringworm

Drug Facts

Active ingredient

Clotrimazole 1%

Purpose

Antifungal

Uses

- cures most ringworm
- relieves itching, redness, irritation and discomfort which accompany this condition

Warnings

For external use only

When using this productavoid contact with eyes

Stop use and ask a doctor if

- irritation occurs
- there is no improvement within 4 weeks

DO NOT USE

Do not useon children under 2 years of age unless directed by a doctor.

Keep out of reach of children.If swallowed, get medical help or contact a Poison Control Center right away.

Directions

- wash affected area and dry thoroughly
- apply a thin layer over affected area twice daily (morning and night)
- supervise children in the use of this product
- use daily for 4 weeks
- if condition persists longer, ask a doctor
- this product is not effective on the scalp or nails

Other information

- To open: unscrew cap, use the pointed end of cap to puncture seal.
- store between 20°- 25°C (68° - 77°F)
- see carton or tube crimp for lot number and expiration date

Inactive ingredients

benzyl alcohol (1%), cetostearyl alcohol, cetyl esters wax, 2-octyldodecanol, polysorbate 60, purified water, sorbitan monostearate

Questions?

Call 1-866-923-4914

DISTRIBUTED BY:
RITE AID, 30 HUNTER LANE,
CAMP HILL, PA 17011

PRINCIPAL DISPLAY PANEL - 14.2 g Tube Carton

RITE
AID®
PHARMACY

Ringworm Cream

Clotrimazole Cream USP, 1%

ANTIFUNGAL

NET WT 0.5 OZ (14.2 g)